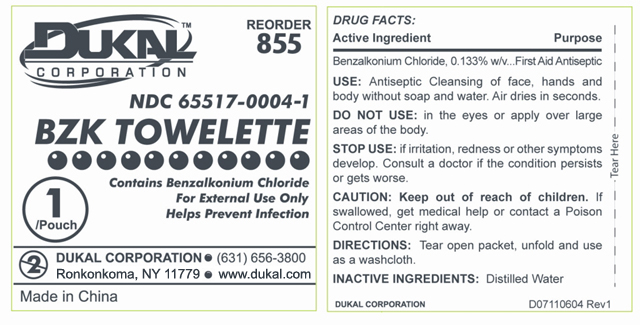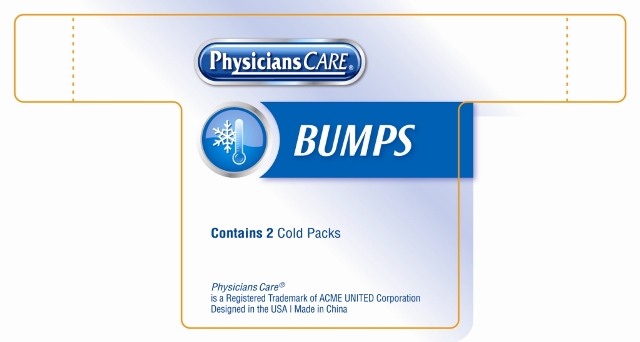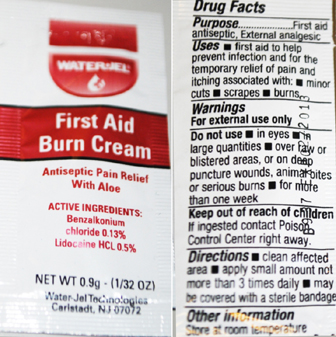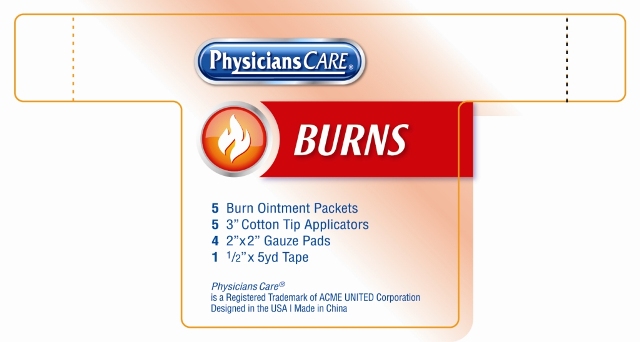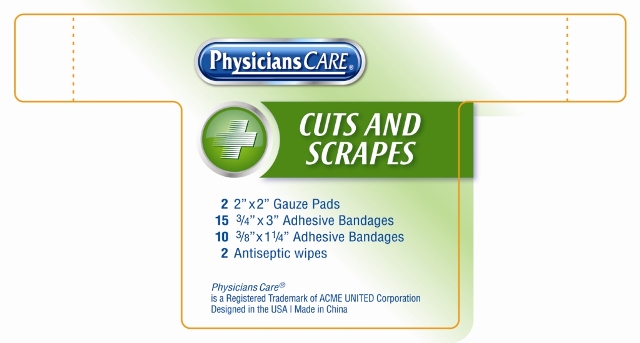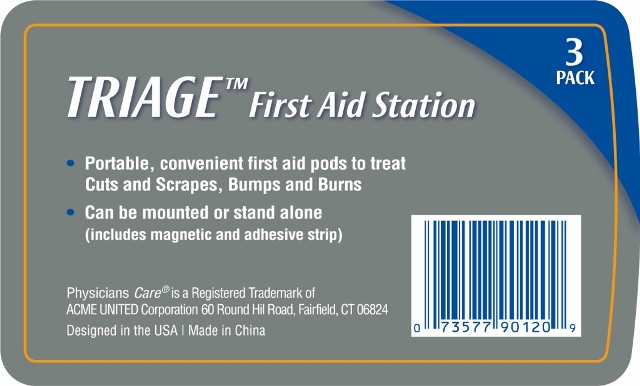 DRUG LABEL: Triage First Aid Station
NDC: 65517-0019 | Form: KIT | Route: TOPICAL
Manufacturer: Dukal Corporation
Category: other | Type: MEDICAL DEVICE
Date: 20100920

ACTIVE INGREDIENTS: BENZALKONIUM CHLORIDE 0.00186 mL/1.4 mL; BENZALKONIUM CHLORIDE 0.13 g/100 g; LIDOCAINE HYDROCHLORIDE 0.5 g/100 g
INACTIVE INGREDIENTS: WATER 1.39814 mL/1.4 mL; EDETATE DISODIUM; LIGHT MINERAL OIL; STEARIC ACID; POLYETHYLENE GLYCOL; CETYL ALCOHOL; TROLAMINE; GLYCERIN; METHYLPARABEN; PROPYLENE GLYCOL; DIAZOLIDINYL UREA; ALOE VERA LEAF; WATER; PROPYLPARABEN; GLYCERYL MONOSTEARATE

Package Labeling

PACKAGE LABEL

TRIAGE First Aid Station

3 PACK

Portable, convenient first aid pods to treat
Cuts and Scrapes, Bumps and Burns

Can be mounted or stand alone
(includes magnetic and adhesive strip)

Physicians Care® is a Registered Trademark of
ACME UNITED Corporation 60 Round Tree Hill Road, Fairfield CT 06824
Designed in the USA | Made in China

CUTS AND SCRAPES Labeling

Physicians Care

CUTS AND SCRAPES

2 2" x 2" Gauze Pads

15 ^3/4" x 3" Adhesive Bandages

10 ^3/8" x 1 ^1/4" Adhesive Bandages

2 Antiseptic Wipes

Physicians Care®
is a Registered Trademark of
ACME UNITED Corporation 60 Round Tree Hill Road, Fairfield CT 06824
Designed in the USA | Made in China

BUMPS Labeling

Physicians Care

BUMPS

Contains 2 Cold Packs

Physicians Care®
is a Registered Trademark of
ACME UNITED Corporation 60 Round Tree Hill Road, Fairfield CT 06824
Designed in the USA | Made in China

BURNS Labeling

Physicians Care

BURNS

5 Burn Ointment Packets

5 3" Cotton Tip Applicators

4 2" x 2" Gauze Pads

2 ^1/2" x 5yd Tape

Physicians Care®
is a Registered Trademark of
ACME UNITED Corporation 60 Round Tree Hill Road, Fairfield CT 06824
Designed in the USA | Made in China

BZK Towelette Labeling

Reorder 855

NDC 65517-0004-1

Dukal

BZK TOWELETTE

Contains Benzalkonium Chloride

For External Use Only

Helps Prevent Infection

1 / Pouch

DUKAL CORPORATION

(631) 656-3800

Ronkonkoma, NY 11779 www.dukal.com

Made in China

Drug Facts

Active Ingredients..................... Benzalkonium Chloride 0.133% w/v

Purpose................................. First Aid Antiseptic

USE: Antiseptic Cleansing of face, hands and
body without soap and water. Airs dries in seconds

DO NOT USE: in the eyes or apply over large
areas of the body.

STOP USE: If irritation, redness or other symptoms
develop. Consult a doctor if the conditions persists
or gets worse.

CAUTION: Keep out of reach of children. If
swallowed get medical help or contact a Poison
Control Center right away.

DIRECTIONS: Tear open packet, unfold and use
as a washcloth.

INACTIVE INGREDIENTS: Distilled Water

First Aid Burn Cream Labeling

WaterJel

First Aid Burn Cream

Antiseptic Pain Relief with Aloe

Active Ingredients:

Benzalkonium Chloride 0.13%

Lidocaine HCL 0.5%

Water-Jel Technologies

Carlstadt, NJ 07072

Drug Facts

Purpose

First Aid Antiseptic, External analgesic

Uses

first aid to help prevent infection and for temporary

relief of pain an itching associated with minor cuts,

scrapes, burns

Warnings

For external use only

Do not use

in the eyes

in large quantities over raw or blistered areas or on

deep puncture wounds, animal bites, or serious burns

Keep out of reach of children

if ingested contact Poison Control Center right away

Directions

clean affected area apply a small amount not more

than 3 times daily may be covered with a sterile bandage

Other Information

Store at room temperature